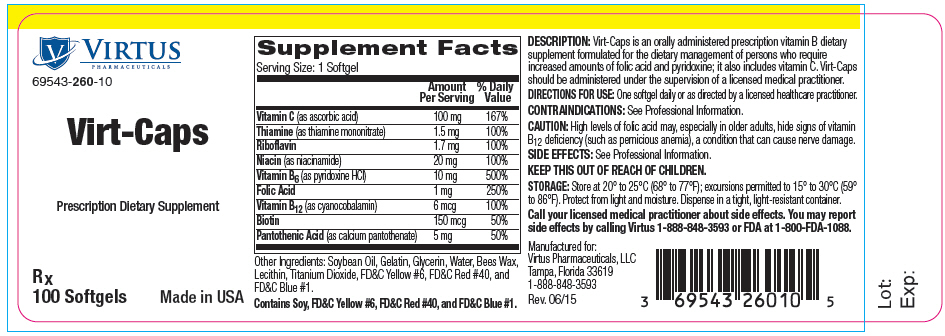 DRUG LABEL: Virt-Caps
NDC: 69543-260 | Form: CAPSULE
Manufacturer: Virtus Pharmaceuticals
Category: other | Type: DIETARY SUPPLEMENT
Date: 20150824

ACTIVE INGREDIENTS: ASCORBIC ACID 100 mg/1 1; THIAMINE MONONITRATE 1.5 mg/1 1; RIBOFLAVIN 1.7 mg/1 1; NIACINAMIDE 20 mg/1 1; PYRIDOXINE HYDROCHLORIDE 10 mg/1 1; FOLIC ACID 1 mg/1 1; CYANOCOBALAMIN 6 ug/1 1; BIOTIN 150 ug/1 1; CALCIUM PANTOTHENATE 5 mg/1 1
INACTIVE INGREDIENTS: SOYBEAN OIL; GELATIN; GLYCERIN; WATER; YELLOW WAX; TITANIUM DIOXIDE; FD&C YELLOW NO. 6; FD&C RED NO. 40; FD&C BLUE NO. 1

Virt-Caps

HEALTH CLAIM

69543-260-10

Rx

Prescription Dietary Supplement

DESCRIPTION

Virt-Caps is an orally administered prescription vitamin B dietary supplement formulated for the dietary management of persons who require increased amounts of folic acid and pyridoxine; it also includes vitamin C. Virt-Caps should be administered under the supervision of a licensed medical practitioner.

Supplement Facts
Serving Size: 1 Softgel
 | Amount Per Serving | % Daily Value
Vitamin C (as ascorbic acid) | 100 mg | 167%
Thiamine (as thiamine mononitrate) | 1.5 mg | 100%
Riboflavin | 1.7 mg | 100%
Niacin (as niacinamide) | 20 mg | 100%
Vitamin B6 (as pyridoxine HCl) | 10 mg | 500%
Folic Acid | 1 mg | 250%
Vitamin B12 (as cyanocobalamin) | 6 mcg | 100%
Biotin | 150 mcg | 50%
Pantothenic Acid (as calcium pantothenate) | 5 mg | 50%

Other Ingredients: Soybean Oil, Gelatin, Glycerin, Water, Bees Wax, Lecithin, Titanium Dioxide, FD&C Yellow #6, FD&C Red #40, and FD&C Blue #1.

Contains Soy, FD&C Yellow #6, FD&C Red #40 and FD&C Blue #1.

Side Effects

Allergic reactions have been reported following the use of oral folate.

Mild transient diarrhea, polycythemia vera, itching, transitory exanthema and the feeling of swelling of the entire body has been associated with cobalamin.

Paresthesia, somnolence, nausea, and headaches have been reported with pyridoxine.

KEEP THIS PRODUCT OUT OF THE REACH OF CHILDREN.

INTERACTIONS

Drugs which may interact with folate include but are not limited to:

- First generation anticonvulsants (folate may reduce their effectiveness)
- Capecitabine (folate may enhance its toxicity)
- Fluorouracil (folate may enhance its toxicity)

Drugs that may interfere with folate metabolism include, but are not limited to:

- Dihydrofolate Reductase Inhibitors
- Fluoxetine
- Nonsteroidal Anti-inflammatory Drugs
- Sulfasalazine
- Warfarin

Drugs which may interfere with the absorption of folate from the gastrointestinal tract or decrease plasma levels include, but are not limited to:

- Cholestyramine
- Colestipol
- Colchicine
- Levodopa
- Cycloserine
- Isotretinoin
- Oral Contraceptives
- Methylprednisolone
- Pancreatic Enzymes
- Pentamidine
- Smoking and Alcohol
- Sulfasalazine
- Metformin

Drugs which may interact with vitamin B6 include, but are not limited to:

- Levodopa (the action of levodopa may be antagonized by vitamin B6.)

Drugs which may interact with vitamin B12 include, but are not limited to:

- Antibiotics, cholestyramine, colchicine, colestipol, metformin, para-aminosalicylic acid, and potassium chloride (may decrease the absorption of vitamin B12)
- Nitrous oxide (can produce a functional vitamin B12 deficiency)

CONTRAINDICATIONS

This product is contraindicated in patients with a known hypersensitivity to any of its components.

CAUTION

High levels of folic acid may, especially in older adults, hide signs of vitamin B12 deficiency (such as pernicious anemia), a condition that can cause nerve damage.

PREGNANCY and NURSING MOTHERS

This product contains only B and C vitamins and is not intended for use as a prenatal/postnatal multivitamin.

DIRECTIONS FOR USE

One softgel daily or as directed by a licensed medical practitioner.

STORAGE

Store at 20° to 25°C (68° to 77°F); excursions permitted to 15° to 30°C (59° to 86°F). Protect from light and moisture. Dispense in a tight, light-resistant container. Notice: Contact with moisture may produce surface discoloration or erosion.

HOW SUPPLIED

Virt-Caps is supplied as black softgels imprinted on one side with "V260" dispensed in child-resistant bottles of 100 softgels

69543-260-10

KEEP THIS OUT OF REACH OF CHILDREN.

All prescriptions using this product shall be pursuant to state statutes as applicable. This is not an Orange Book product.

Call your medical practitioner about side effects. You may report side effects by calling Virtus at 1-888-848-3593 or FDA at 1-800-FDA-1088.

Rx

Manufactured for:
Virtus Pharmaceuticals, LLC
Tampa, Florida 33619
1-888-848-3593

MADE IN USA

Rev. 06/2015

PRINCIPAL DISPLAY PANEL - 100 Capsule Bottle Label

VIRTUS
PHARMACEUTICALS

69543-260-10

Virt-Caps

Prescription Dietary Supplement

Rx
100 Softgels
Made in USA